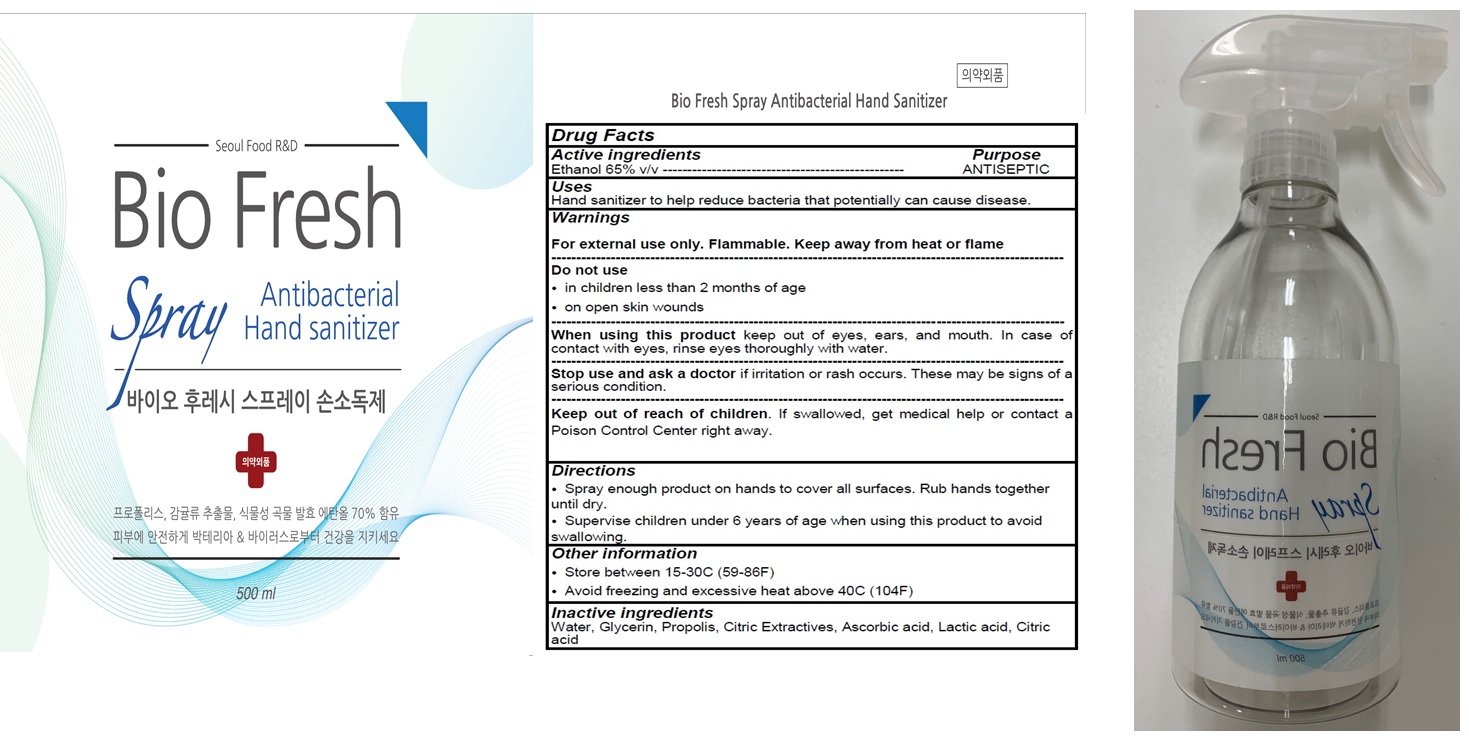 DRUG LABEL: Bio Fresh Antibacterial Hand Sanitizer
NDC: 71059-050 | Form: SPRAY
Manufacturer: KONEL
Category: otc | Type: HUMAN OTC DRUG LABEL
Date: 20200612

ACTIVE INGREDIENTS: ALCOHOL 65 mL/100 mL
INACTIVE INGREDIENTS: Glycerin; PROPOLIS WAX; Ascorbic acid; LACTIC ACID, UNSPECIFIED FORM; CITRIC ACID MONOHYDRATE

ACTIVE INGREDIENT

Ethanol 65% v/v

INACTIVE INGREDIENTS

Water, Glycerin, Propolis, Citric Extractives, Ascorbic acid, Lactic acid, Citric acid

PURPOSE

ANTISEPTIC

WARNINGS

For external use only. Flammable. Keep away from heat or flame
--------------------------------------------------------------------------------------------------------
Do not use
• in children less than 2 months of age
• on open skin wounds
--------------------------------------------------------------------------------------------------------
When using this product keep out of eyes, ears, and mouth. In case of contact with eyes, rinse eyes thoroughly with water.
--------------------------------------------------------------------------------------------------------
Stop use and ask a doctor if irritation or rash occurs. These may be signs of a serious condition.

KEEP OUT OF REACH OF CHILDREN

If swallowed, get medical help or contact a Poison Control Center right away.

Use

Hand sanitizer to help reduce bacteria that potentially can cause disease.

Directions

• Spray enough product on hands to cover all surfaces. Rub hands together until dry.
• Supervise children under 6 years of age when using this product to avoid swallowing.

Other information

• Store between 15-30C (59-86F)
• Avoid freezing and excessive heat above 40C (104F)